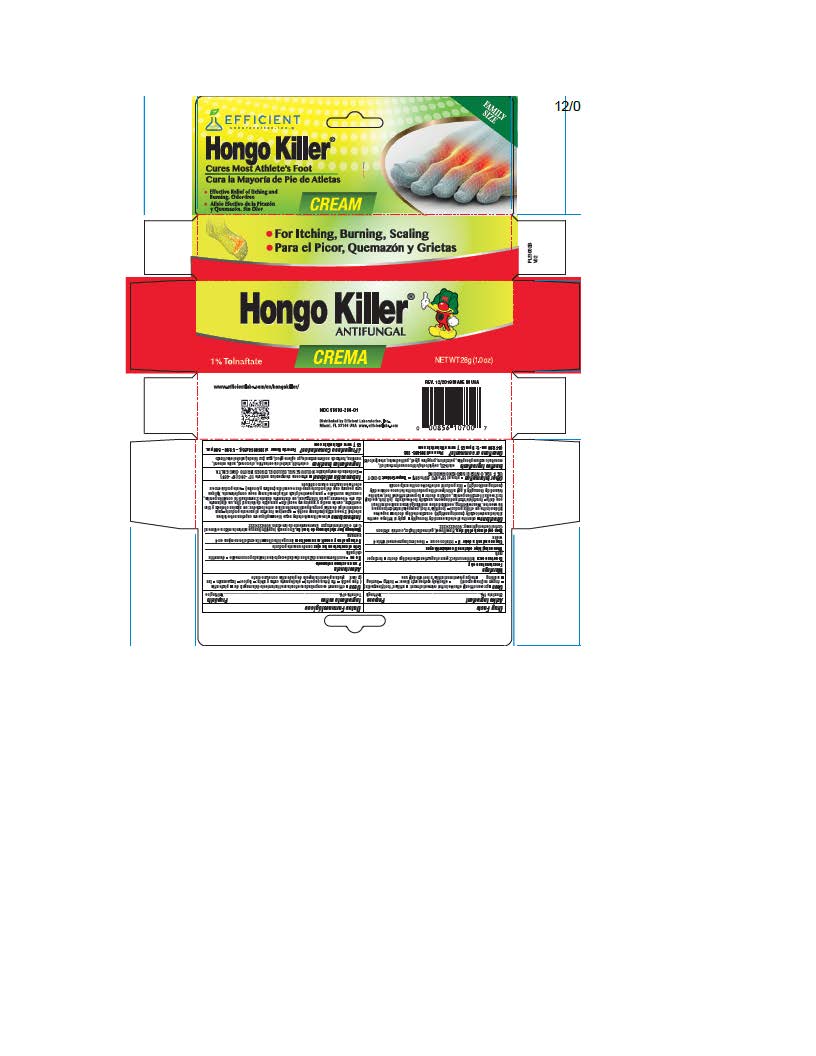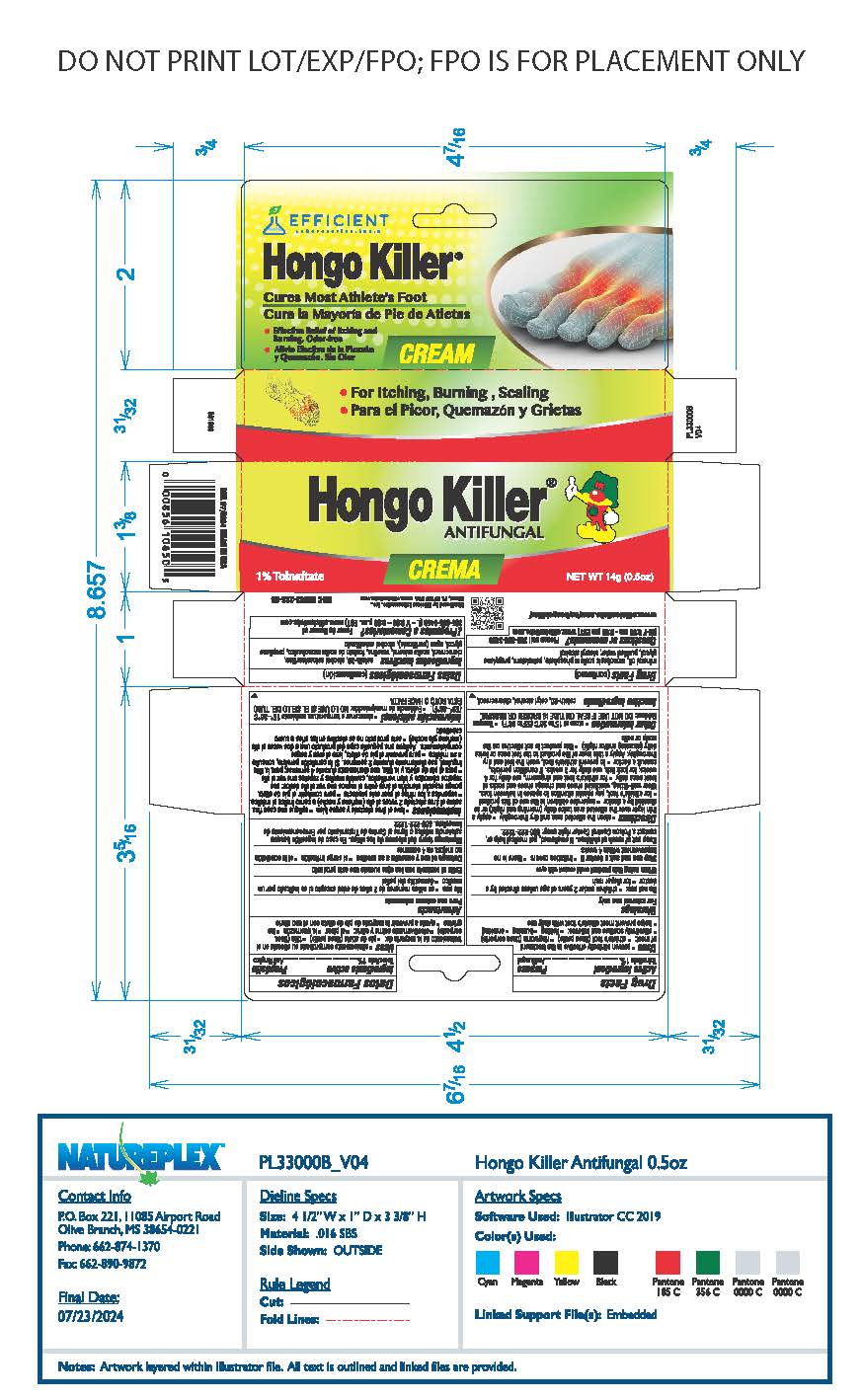 DRUG LABEL: Hongo Killer
NDC: 58593-286 | Form: CREAM
Manufacturer: Efficient Laboratories Inc
Category: otc | Type: HUMAN OTC DRUG LABEL
Date: 20241014

ACTIVE INGREDIENTS: TOLNAFTATE 10 mg/1 g
INACTIVE INGREDIENTS: STEARYL ALCOHOL; CETYL ALCOHOL; SODIUM PHOSPHATE, MONOBASIC; CETETH-20; CHLOROCRESOL; MINERAL OIL; PROPYLENE GLYCOL; WATER; PETROLATUM

Hongo Killer®

Drug Facts

Active ingredient

Tolnaftate 1%

Purpose

Antifungal

Uses

proven clinically effective in the treatment of most:

- athlete's foot (tinea pedis)
- ringworm (tinea corporis)
- effectively soothes are relieves:
- itching
- burning
- cracking
- helps prevent most athlete's foot with daily use

Warnings

For external use only.

Do not use on children under 2 years of age unless directed by a doctor

For Diaper Rash

When using this product avoid contact with eyes

Stop use and ask a doctor if

- irritation occurs
- there is no improvement within 4 weeks

Keep out of reach of children. If swallowed, get medical help or, contact a Poison Control Center right away: 800-222-1222.

Directions

- clean the affected area and dry thoroughly
- apply a thin layer over the affected area twice daily (morning and night) or as directed by a doctor
- supervise children in the use of this product
- for athlete's foot, pay special attention to spaces between the toes. Wear well-fitting, ventilated shoes, and change shoes and socks at least once daily
- for athlete's foot and ringworm, use daily for 4 weeks; for jock itch, use daily for 2 weeks. If condition persists, consult a doctor
- to prevent athlete's foot, wash the feet, and dry thoroughly. Apply a thin layer over the affected area twice daily (morning and/or night)
- this product is not effective on scalp or nails

Other information

- store at 15°to 30°C (59°to 86°F)
- Tamper Evident: DO NOT USE IF SEAL ON TUBE IS BROKEN OR MISSING.

Inactive ingredients

ceteth-20, cetyl alcohol, chlorocresol, mineral oil, monobasic sodium phosphate, petrolatum, propylene glycol, purified water, stearyl alcohol

Questions or comments?

Please call 305-805-3456
(M-F 9:00 am-5:00 pm EST www.efficientlabs.com

Distributed by Efficient Laboratories, Inc.,
Miami, FL 33166 USA